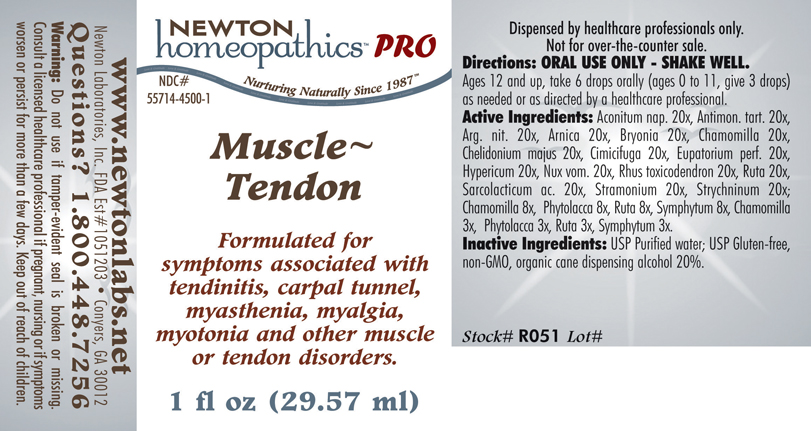 DRUG LABEL: Muscle - Tendon 
NDC: 55714-4500 | Form: LIQUID
Manufacturer: Newton Laboratories, Inc.
Category: homeopathic | Type: HUMAN PRESCRIPTION DRUG LABEL
Date: 20110601

ACTIVE INGREDIENTS: Aconitum Napellus 20 [hp_X]/1 mL; Antimony Potassium Tartrate 20 [hp_X]/1 mL; Silver Nitrate 20 [hp_X]/1 mL; Arnica Montana 20 [hp_X]/1 mL; Bryonia Alba Root 20 [hp_X]/1 mL; Matricaria Recutita 20 [hp_X]/1 mL; Chelidonium Majus 20 [hp_X]/1 mL; Black Cohosh 20 [hp_X]/1 mL; Eupatorium Perfoliatum Flowering Top 20 [hp_X]/1 mL; Hypericum Perforatum 20 [hp_X]/1 mL; Strychnos Nux-vomica Seed 20 [hp_X]/1 mL; Toxicodendron Pubescens Leaf 20 [hp_X]/1 mL; Ruta Graveolens Flowering Top 20 [hp_X]/1 mL; Lactic Acid, L- 20 [hp_X]/1 mL; Datura Stramonium 20 [hp_X]/1 mL; Strychnine 20 [hp_X]/1 mL; Phytolacca Americana Root 8 [hp_X]/1 mL; Comfrey Root 8 [hp_X]/1 mL
INACTIVE INGREDIENTS: Alcohol

Muscle - Tendon

INDICATIONS & USAGE SECTION

Muscle - Tendon Formulated for symptoms associated with tendinitis, carpal tunnel, myasthenia, myalgia, myotonia and other muscle or tendon disorders.

DOSAGE & ADMINISTRATION SECTION

Directions: ORAL USE ONLY - SHAKE WELL. Ages 12 and up, take 6 drops orally (ages 0 to 11, give 3 drops) as needed or as directed by a healthcare professional.

ACTIVE INGREDIENT SECTION

Aconitum nap. 20x, Antimon. tart. 20x, Arg. nit. 20x, Arnica 20x, Bryonia 20x, Chamomilla 20x, Chelidonium majus 20x, Cimicifuga 20x, Eupatorium perf. 20x, Hypericum 20x, Nux vom. 20x, Rhus toxicodendron 20x, Ruta 20x, Sarcolacticum ac. 20x, Stramonium 20x, Strychninum 20x, Chamomilla 8x, Phytolacca 8x, Ruta 8x, Symphytum 8x, Chamomilla 3x, Phytolacca 3x, Ruta 3x, Symphytum 3x.

PURPOSE SECTION

Formulated for symptoms associated with tendinitis, carpal tunnel, myasthenia, myalgia, myotonia and other muscle or tendon disorders.

INACTIVE INGREDIENT SECTION

Inactive Ingredients: USP Purified Water; USP Gluten-free, non-GMO, organic cane dispensing alcohol 20%.

QUESTIONS? SECTION

www.newtonlabs.net Newton Laboratories, Inc. FDA Est # 1051203 - Conyers, GA 30012
Questions? 1.800.448.7256

WARNINGS SECTION

Warning: Do not use if tamper - evident seal is broken or missing. Consult a licensed healthcare professional if pregnant, nursing or if symptoms worsen or persist for more than a few days. Keep out of reach of children.

PREGNANCY OR BREAST FEEDING SECTION

Consult a licensed healthcare professional if pregnant, nursing or if symptoms worsen or persist for more than a few days.

KEEP OUT OF REACH OF CHILDREN SECTION

Keep out of reach of children.